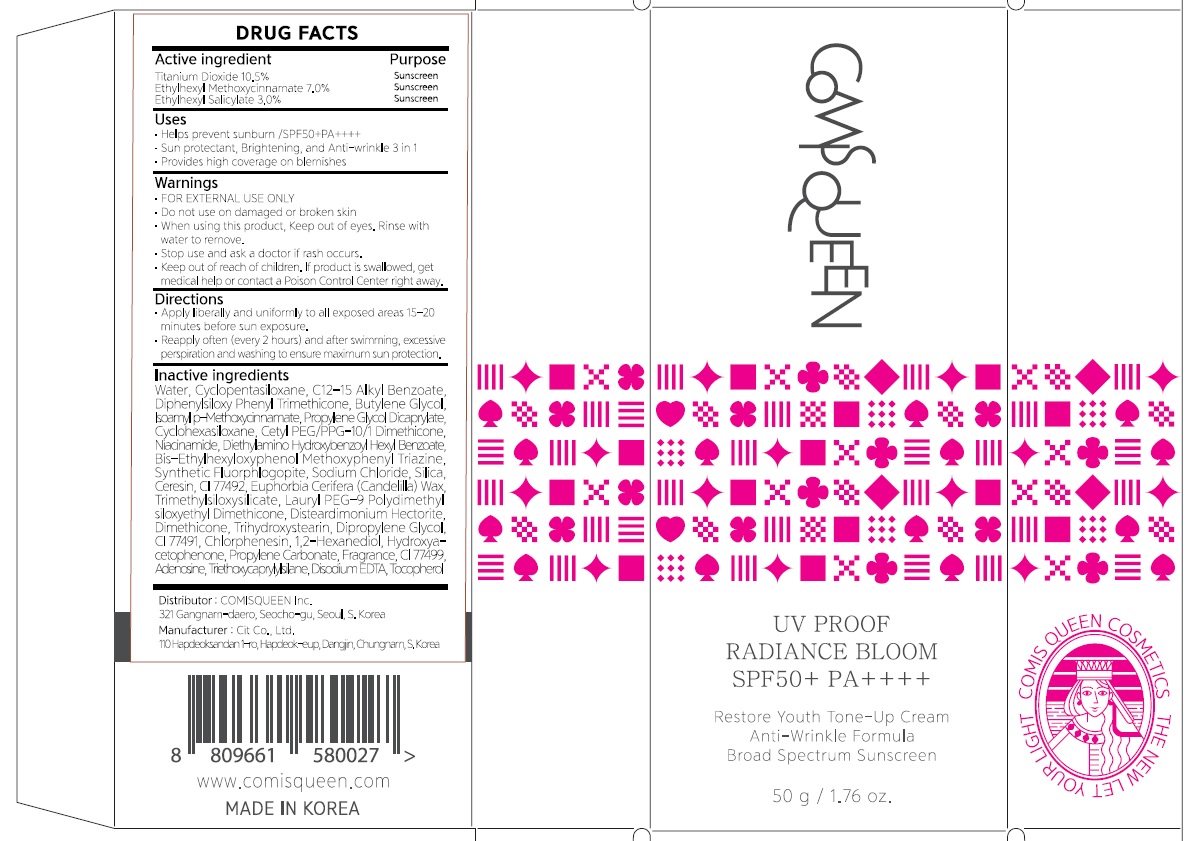 DRUG LABEL: COMISQUEEN UV PROOF RADIANCE BLOOM
NDC: 82759-010 | Form: CREAM
Manufacturer: COMIS QUEEN Inc.
Category: otc | Type: HUMAN OTC DRUG LABEL
Date: 20220603

ACTIVE INGREDIENTS: Titanium Dioxide 10.5 g/100 g; Octinoxate 7.0 g/100 g; Octisalate 3.0 g/100 g
INACTIVE INGREDIENTS: Water; CYCLOMETHICONE 5; ALKYL (C12-15) BENZOATE

ACTIVE INGREDIENT

Titanium Dioxide 10.5%
Ethylhexyl Methoxycinnamate 7.0%
Ethylhexyl Salicylate 3.0%

INACTIVE INGREDIENTS

Water, Cyclopentasiloxane, C12-15 Alkyl Benzoate, Diphenylsiloxy Phenyl Trimethicone, ButyleneGlycol,IsoamylpMethoxycinnamate,PropyleneGlycolDicaprylate,Cyclohexasiloxane,Cetyl PEG/PPG-10/1 Dimethicone, Niacinamide, Diethylamino Hydroxybenzoyl Hexyl Benzoate, Bis-Ethylhexyloxyphenol Methoxyphenyl Triazine, Synthetic Fluorphlogopite, Sodium Chloride, Silica, Ceresin, CI 77492, Euphorbia Cerifera (Candelilla) Wax, Trimethylsiloxysilicate, Lauryl PEG-9 Polydimethylsiloxyethyl Dimethicone, Disteardimonium Hectorite, Dimethicone, Trihydroxystearin, Dipropylene Glycol, CI 77491, Chlorphenesin, 1,2-Hexanediol, Hydroxyacetophenone, Propylene Carbonate, Fragrance, CI 77499, Adenosine, Triethoxycaprylylsilane, Disodium EDTA, Tocopherol

PURPOSE

Sunscreen

WARNINGS

■ FOR EXTERNAL USE ONLY
■ Do not use on damaged or broken skin
■ When using this product, Keep out of eyes. Rinse with water to remove.
■ Stop use and ask a doctor if rash occurs.
■ Keep out of reach of children. If product is swallowed, get medical help or contact a Poison Control Center right away.

■ Keep out of reach of children. If product is swallowed, get medical help or contact a Poison Control Center right away.

Uses

■ Helps prevent sunburn /SPF50+PA++++

■ Sun protectant, Brightening,,and Anti-wrinkle 3 in 1-
■ Provides high coverage on blemishes

Directions

■ Apply liberally and uniformly to all exposed areas 15-20 minutes before sun exposure.

■ Reapply often (every 2 hours) and after swimming, excessive perspiration and washing to ensure maximum sun protection.